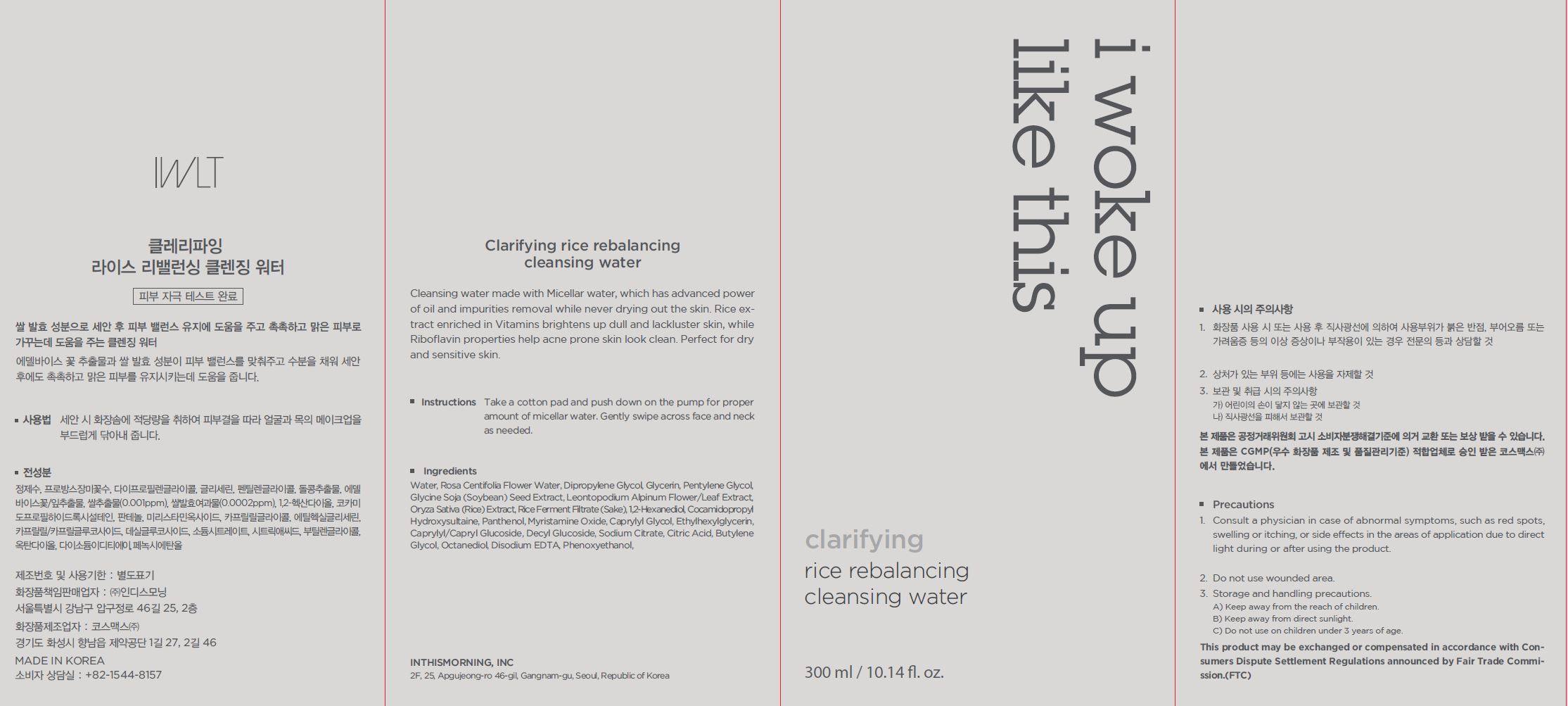 DRUG LABEL: Claritying rice rebalancing cleansing water
NDC: 71217-0065 | Form: LIQUID
Manufacturer: inthismorning co ltd
Category: otc | Type: HUMAN OTC DRUG LABEL
Date: 20230131

ACTIVE INGREDIENTS: RICE GERM 0.0000001 g/100 mL
INACTIVE INGREDIENTS: WATER; GLYCERIN

Drug Facts

ACTIVE INGREDIENT

Oryza Sativa (Rice) Extract

INACTIVE INGREDIENT

Water
Rosa Centifolia Flower Water
Dipropylene Glycol
Glycerin
Pentylene Glycol
1,2-Hexanediol
Cocamidopropyl Hydroxysultaine
Panthenol
Myristamine Oxide
Caprylyl Glycol
Ethylhexylglycerin
Phenoxyethanol
Caprylyl/Capryl Glucoside
Decyl Glucoside
Sodium Citrate
Citric Acid
Disodium EDTA
Glycine Soja (Soybean) Seed Extract
Butylene Glycol
Octanediol
Leontopodium Alpinum Flower/Leaf Extract
Rice Ferment Filtrate (Sake)

PURPOSE

moisturizing

keep out or reach of the children

INDICATIONS AND USAGE

take a cotton pad and push down on the pump for proper amount of micellar water, gently swipe across face and neck as needed

WARNINGS

This product is for exeternal use only. Do not use for internal use
Storage and handling precautions
If possible, avoid direct sunlight and store in cool and area of low humidity in order to maintain the quality of the product and avoid misuse
Avoid placing the product near fire and store out in reach of children

- consult a physician in case of abnormal symptoms, such as red spots, swelling or itching, or side effects in the areas of application due to direct light during or after using the product

- do not use on wounded area

DOSAGE AND ADMINISTRATION

for external use only